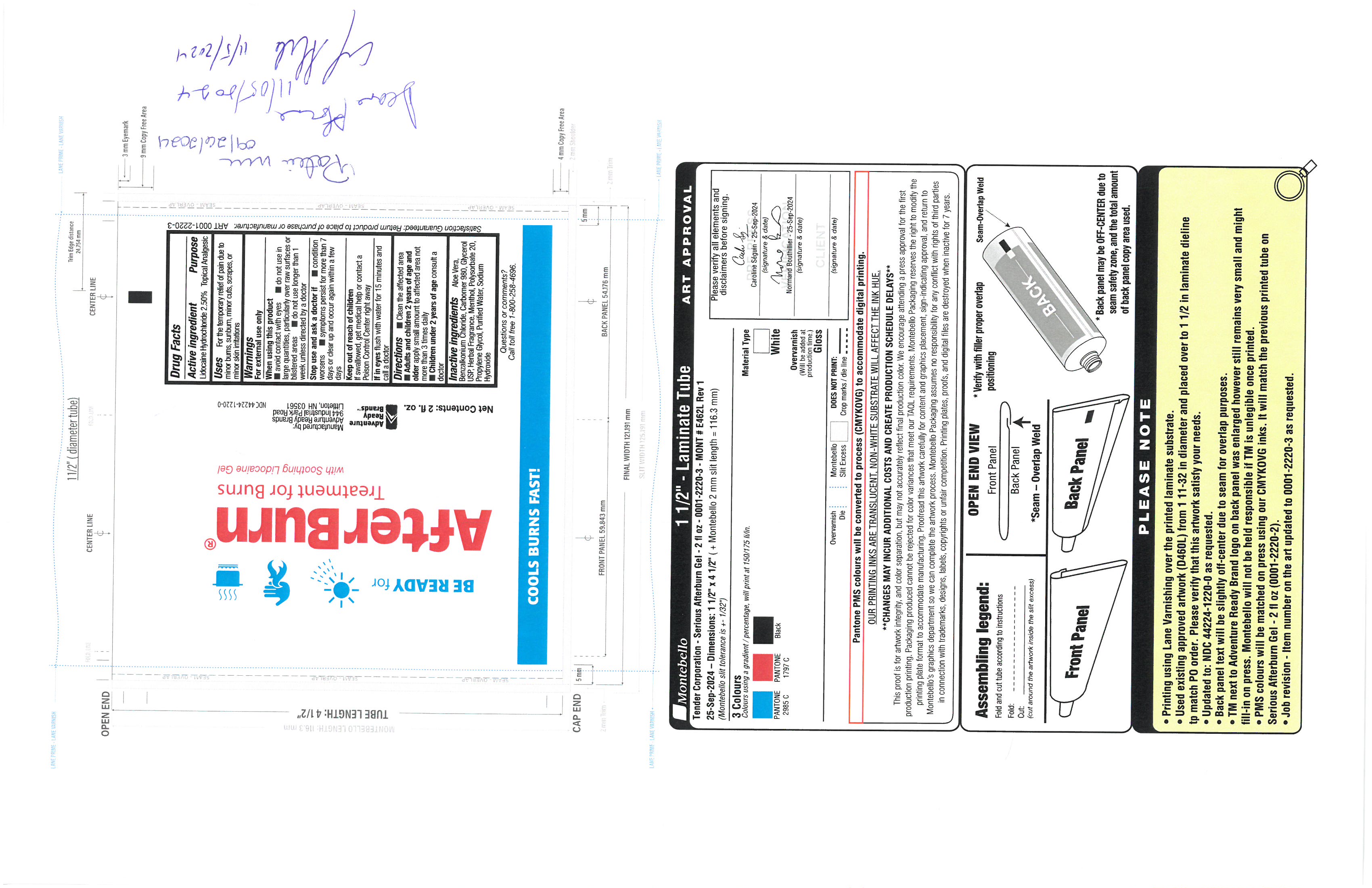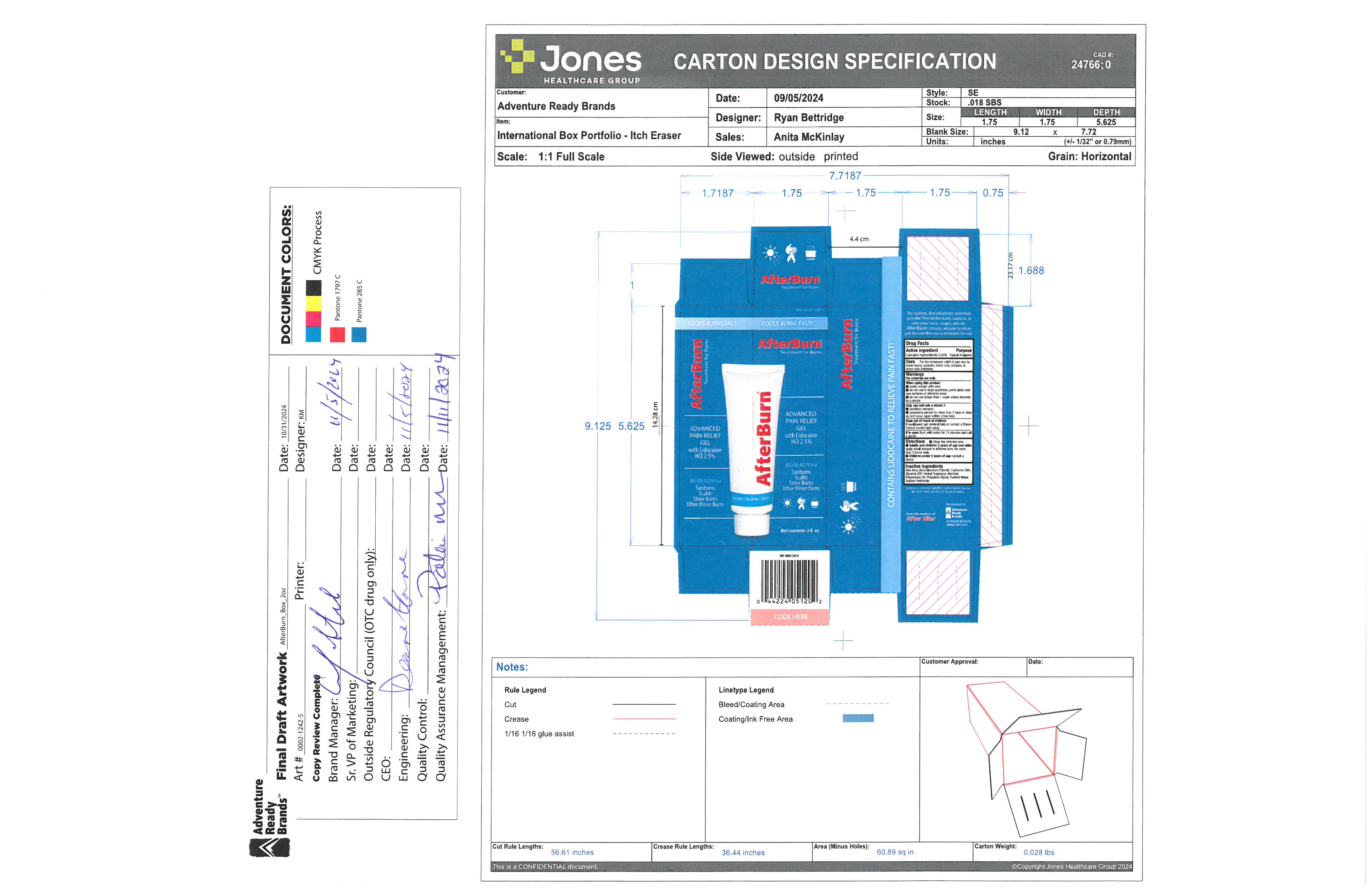 DRUG LABEL: After Burn
NDC: 44224-1220 | Form: GEL
Manufacturer: Tender Corporation d/b/a Adventure Ready Brands
Category: otc | Type: HUMAN OTC DRUG LABEL
Date: 20251218

ACTIVE INGREDIENTS: LIDOCAINE HYDROCHLORIDE ANHYDROUS 1.425 g/57 g
INACTIVE INGREDIENTS: GLYCERIN 1.14 g/57 g; WATER 44.3 g/57 g; BENZALKONIUM CHLORIDE 0.0015 g/57 g; CARBOMER HOMOPOLYMER, UNSPECIFIED TYPE 0.57 g/57 g; POLYSORBATE 20 1.14 g/57 g; SODIUM HYDROXIDE 0.57 g/57 g; MENTHOL 0.057 g/57 g; CARBOMER 980 5.7 g/57 g; PROPYLENE GLYCOL 2.85 g/57 g; ALOE VERA LEAF JUICE 4.56 g/57 g

After Burn

Active Ingredient

Lidocaine Hydrochloride 2.50%

Purpose

Topical Analgesic

Uses

For the temporary relief of pain due to minor burns, sunburns, minor cuts, scrapes, or minor skin irritations

Warnings

for external use only

When using this product

avoid contact with eyes

do not use in large quantities, particularly over raw surfaces or blistered areas

do not use longer than 1 week unless directed by doctor

Stop Use and ask a doctor if

Condition worsens

Symptoms persist for more than 7 days or clear

up and occur again within a few days.

Keep out of reach of children

if swallowed, get medical help or contact poisn control center right away.

If in eyes

flush with water for 15 minutes and call a doctor

Directions

Clean rg affected area.

Adults and children 2 years of age and older apply a small amount to affected area not more than 3 times daily.

Children under 2 years of age consult a doctor

Inactive Ingredients

Aloe Vera, Benzalkonium Chloride, Carbomer 980, GLycerol USP, Herbal Fragrance, Menthol, Polysorbate 20, Propylene Glycol, Purified Water, Sodium Hydroxide